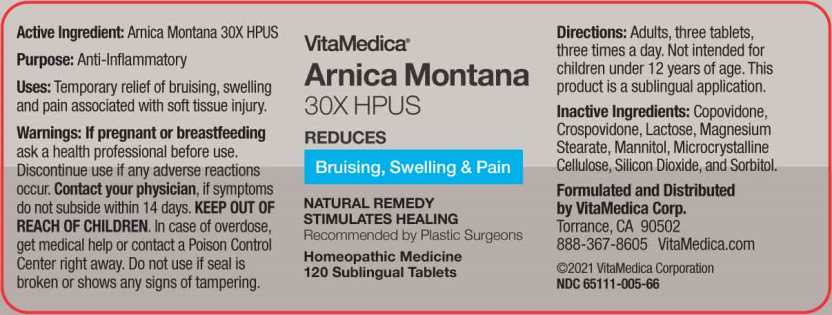 DRUG LABEL: Arnica Montana
NDC: 65111-005 | Form: TABLET
Manufacturer: Vitamedica Corporation
Category: homeopathic | Type: HUMAN OTC DRUG LABEL
Date: 20240213

ACTIVE INGREDIENTS: ARNICA MONTANA WHOLE 30 [hp_X]/1 1
INACTIVE INGREDIENTS: LACTOSE; MAGNESIUM STEARATE; MANNITOL; CELLULOSE, MICROCRYSTALLINE; SORBITOL; SILICON DIOXIDE; CROSPOVIDONE; COPOVIDONE

Drug Facts

ACTIVE INGREDIENT:

Arnica Montana 30X.

PURPOSE:

Anti-Inflammatory

WARNINGS:

If pregnant or breast-feeding ask a health professional before use. Discontinue use if any adverse reactions occur. Contact your physician, if symptoms do not subside within 14 days.

KEEP OUT OF REACH OF CHILDREN. In case of overdose, get medical help or contact a Poison Control Center right away.

Do not use if seal is broken or shows any signs of tampering.

KEEP OUT OF REACH OF CHILDREN. In case of overdose, get medical help or contact a Poison Control Center right away.

DIRECTIONS:

Adults, three tablets, three times a day. Not intended for children under 12 years of age. This product is a sublingual application.

USES:

Temporary relief of bruising, swelling and pain associated with soft tissue injury.

INACTIVE INGREDIENTS:

Copovidone, Crospovidone, Lactose, Magnesium Stearate, Mannitol, Microcrystalline Cellulose, Silicon Dioxide, and Sorbitol.

QUESTIONS:

Formulated and Distributed

by VitaMedica Corp.

Torrance, CA 90502

888-367-8605 VitaMedica.com

©2021 VitaMedica Corporation

NDC 65111-005-66

PACKAGE DISPLAY LABEL

VitaMedica

Arnica Montana

30X HPUS

REDUCES

Bruising, Swelling & Pain

NATURAL REMEDY

STIMULATES HEALING

Recommended by Plastic Surgeons

Homeopathic Medicine

120 Sublingual Tablets